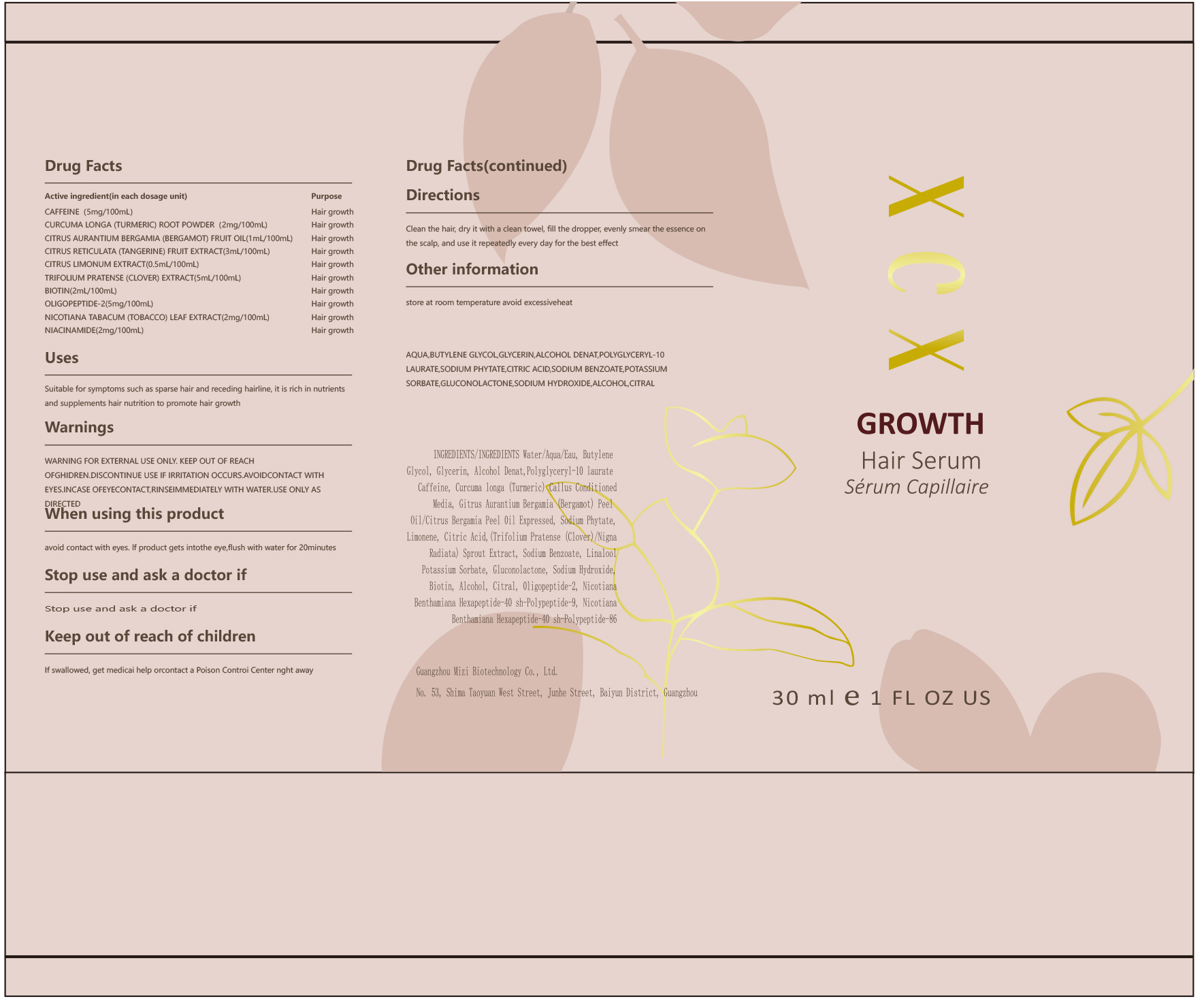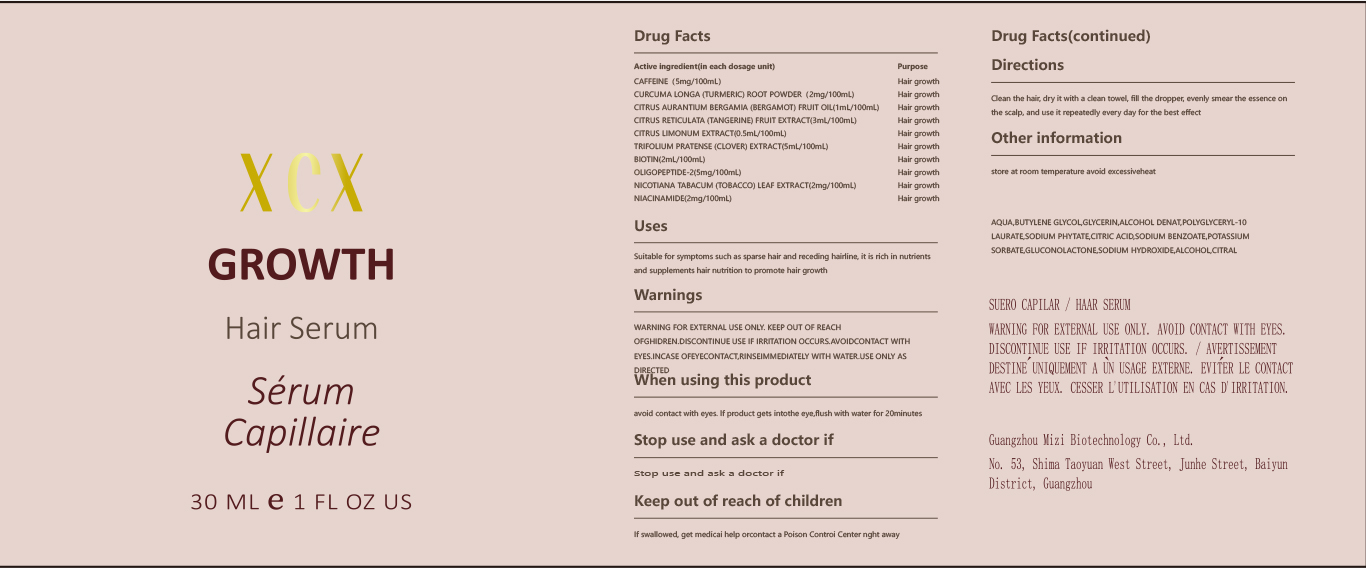 DRUG LABEL: GROWTH Hair Serum Serum Capillaire
NDC: 84952-001 | Form: LIQUID
Manufacturer: Fuzhou Xinbaike Network Technology Service Co., Ltd
Category: otc | Type: HUMAN OTC DRUG LABEL
Date: 20241213

ACTIVE INGREDIENTS: CITRUS TANGERINA (TANGERINE) FRUIT 3 mg/100 mL; LEMON 0.5 mg/100 mL; NICOTIANA BENTHAMIANA WHOLE 2 mg/100 mL; TOBACCO LEAF 2 mg/100 mL; CURCUMA LONGA (TURMERIC) ROOT 2 mg/100 mL; CITRUS AURANTIUM BERGAMIA (BERGAMOT) FRUIT OIL 1 mg/100 mL; TRIFOLIUM PRATENSE LEAF 5 mg/100 mL; BIOTIN 2 mg/100 mL; LYSYLTHREONYLTHREONYLLYSYLSERINE 5 mg/100 mL
INACTIVE INGREDIENTS: GLYCERIN; GLUCONOLACTONE; CITRAL; ALCOHOL; CAFFEINE 5 mg/100 mL; SODIUM HYDROXIDE; SODIUM BENZOATE; WATER; BUTYLENE GLYCOL; ACONITIC ACID; POTASSIUM SORBATE; SODIUM PHYTATE; POLYGLYCERYL-10 LAURATE

GROWTH Hair Serum Serum Capillaire

ACTIVE INGREDIENT

CAFFEINE(5mg/100mL)
CURCUMA LONGA (TURMERIC) ROOT POWDER (2mg/100mL)

CITRUS AURANTIUM BERGAMIA (BERGAMOT) FRUIT OIL(1mg/100mL)

CITRUS RETICULATA (TANGERINE) FRUIT EXTRACT(3mg/100mL)

CITRUS LIMONUM EXTRACT(0.5mg/100mL)

TRIFOLIUM PRATENSE (CLOVER) EXTRACT(5mg/100mL)

BIOTIN(2mg/100mL)
OLIGOPEPTIDE-2(5mg/100mL)

NICOTIANA TABACUM (TOBACCO)

LEAF EXTRACT(2mg/100mL)

NIACINAMIDE(2mg/100mL)

PURPOSE

Hair growth

INDICATIONS AND USAGE

Suitable for symptoms such as sparse hair and receding hairline, it is rich in nutrientsand supplements hair nutrition to promote hair growth

WARNINGS

WARNING FOR EXTERNAL USE ONLY. KEEP OUT OF REACHOFGHIDREN.DISCONTINUE USE IF IRRITATION OCCURS.AVOIDCONTACT WITHEYES.INCASE OFEYECONTACT,RINSEIMMEDIATELY WITH WATER.USE ONLY ASDIRECTED

WHEN USING

avoid contact with eyes. lf product gets intothe eye,flush with water for 20minutes

Stop use and ask a doctor if

KEEP OUT OF REACH OF CHILDREN

If swallowed, get medicai help orcontact a Poison Controi Center nght away

DOSAGE AND ADMINISTRATION

Clean the hair, dry it with a clean towel, fill the dropper, evenly smear the essence onthe scalp, and use it repeatedly every day for the best effect

STORAGE AND HANDLING

store at room temperature avoid excessiveheat

INACTIVE INGREDIENT

AQUA
BUTYLENE GLYCOL
GLYCERIN
ALCOHOL DENAT
POLYGLYCERYL-10 LAURATE
SODIUM PHYTATE
CITRIC ACID
SODIUM BENZOATE
POTASSIUM SORBATE
GLUCONOLACTONE
SODIUM HYDROXIDE
ALCOHOL
CITRAL